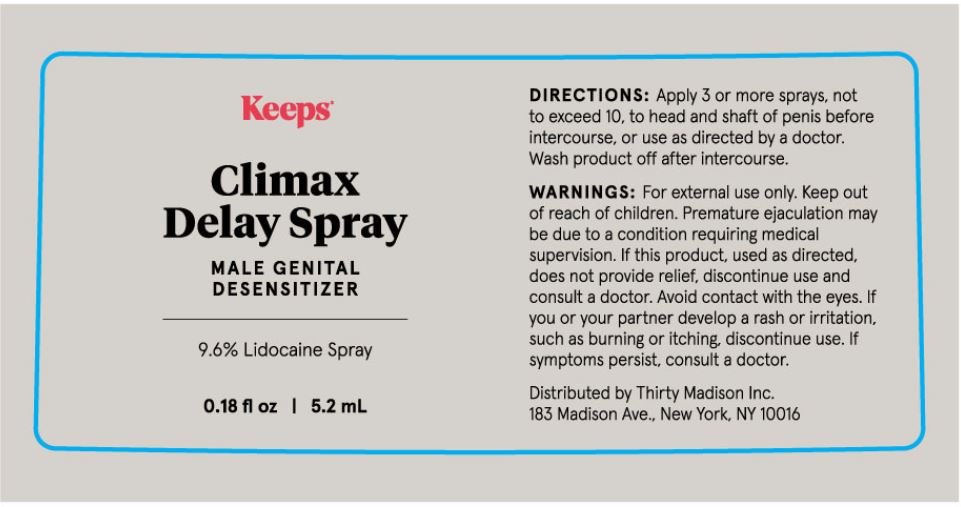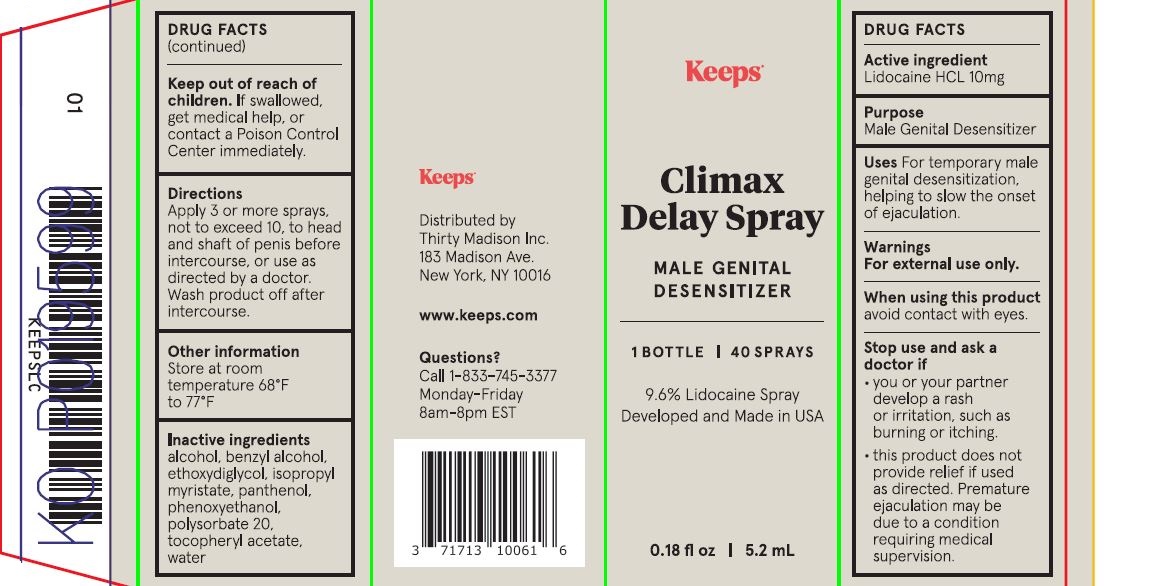 DRUG LABEL: Keeps Climax Delay
NDC: 52261-0801 | Form: LIQUID
Manufacturer: Cosco International, Inc.
Category: otc | Type: HUMAN OTC DRUG LABEL
Date: 20240617

ACTIVE INGREDIENTS: LIDOCAINE HYDROCHLORIDE ANHYDROUS 0.0096 kg/1 kg
INACTIVE INGREDIENTS: ALCOHOL; BENZYL ALCOHOL; DIETHYLENE GLYCOL MONOETHYL ETHER; ISOPROPYL MYRISTATE; PANTHENOL; PHENOXYETHANOL; POLYSORBATE 20; .ALPHA.-TOCOPHEROL ACETATE; WATER

Keeps Climax Delay Spray

Drug Facts

Active Ingredient....................Purpose

Lidocaine HCL 9.6%..................Male Genital Desensitizer

Uses

For temporary male genital desensitization, helping to slow the onset of ejaculation.

Warnings

For external use only.

When using this product

avoid contact with eyes.

Stop use and ask a doctor if

- you or your partner develop a rash or irritation, such as burning or itching.
- this product does not provide relief if used as directeed. Premature ejaculation may be due to a condition requiring medical supervision.

Keep out of reach of children.

If swallowed, get medical help, or contact a Poison Control Center immedieately.

Directions

Apply 3 or more sprays, not to exceed 10, to head and shaft of penis before intercourse, or use as directed by a doctor. Wash product off after intercourse.

Other information

Store at room temperature 68°F to 77°F

Inactive ingredients

Alcohol, Benzyl Alcohol, Ethoxydiglycol, Isopropyl Myristate, Panthenol, Phenoxyethanol, Polysorbate 20, Tocopheryl Acetate, Water

PACKAGE LABEL

Add image transcription here...

Add image transcription here...